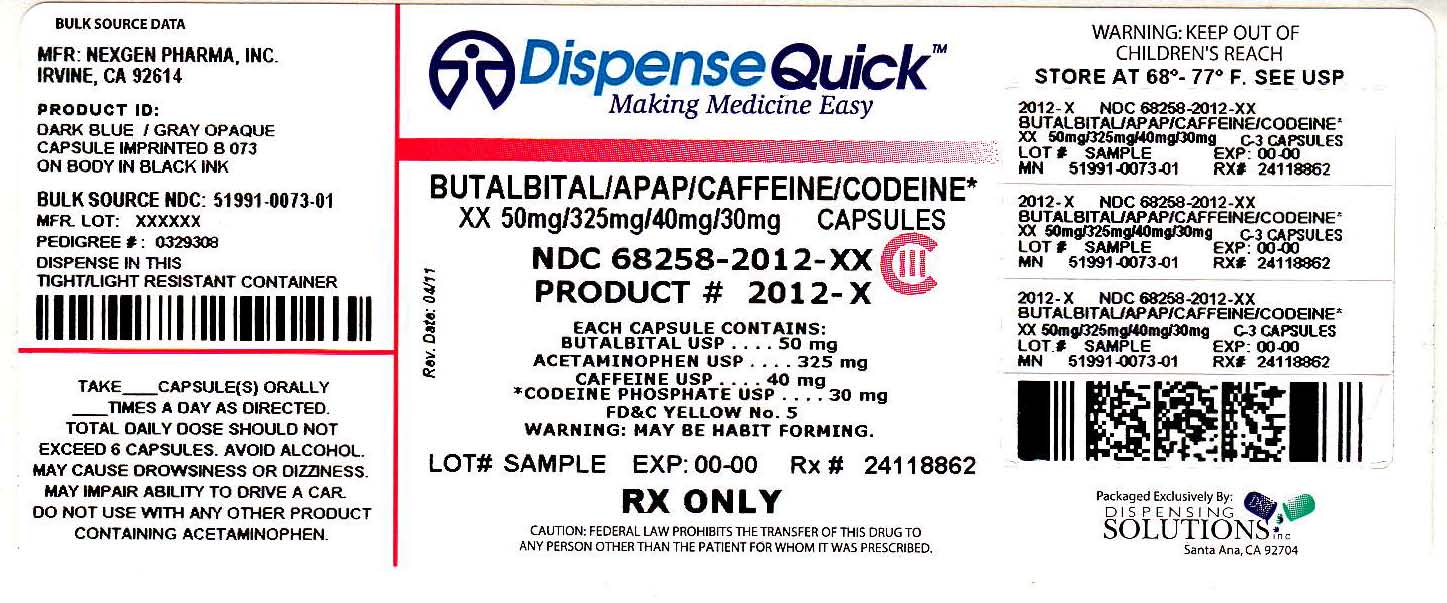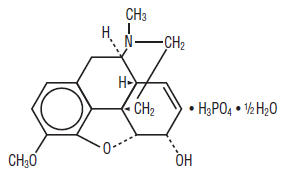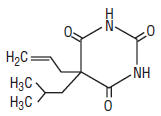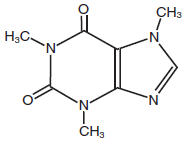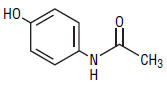 DRUG LABEL: Butalbital, Acetaminophen, Caffeine and Codeine Phosphate
NDC: 68258-2012 | Form: CAPSULE
Manufacturer: Dispensing Solutions, Inc.
Category: prescription | Type: HUMAN PRESCRIPTION DRUG LABEL
Date: 20111003
DEA Schedule: CIII

ACTIVE INGREDIENTS: Butalbital 50 mg/1 1; Acetaminophen 325 mg/1 1; Caffeine 40 mg/1 1; Codeine Phosphate 30 mg/1 1
INACTIVE INGREDIENTS: FD&C Blue No. 1; FD&C Red No. 3; FD&C Red No. 40; FD&C Yellow No. 5; Gelatin; Cellulose, Microcrystalline; Sodium Lauryl Sulfate; Stearic Acid; Talc; Titanium Dioxide

Butalbital, Acetaminophen, Caffeine,
and Codeine Phosphate Capsules
CIII

Rx only

DESCRIPTION

Butalbital, Acetaminophen, Caffeine, and Codeine Phosphate is supplied in capsule form for oral administration.

Each capsule contains the following active ingredients:

Codeine Phosphate, USP ........................................ | 30 mg
Butalbital, USP ........................................................ | 50 mg
Caffeine, USP ......................................................... | 40 mg
Acetaminophen, USP .............................................. | 325 mg

Codeine phosphate [7,8-didehydro-4,5α-epoxy-3-methoxy-17-methylmorphinan-6α-ol phosphate (1:1) (salt) hemihydrate, C18H24N07P, anhydrous mw 397.37], is a narcotic analgesic and antitussive. The structural formula of codeine phosphate is:

Butalbital (5-allyl-5-isobutylbarbituric acid, C11H16N203, mw 224.26), is a short-to intermediate- acting barbiturate. The structural formula of butalbital is:

Caffeine (1,3,7-trimethylxanthine, C8H10N4O2, mw 194.19), is a central nervous system stimulant. The structural formula of caffeine is:

Acetaminophen (4'-hydroxyacetanilide, C8H9NO2, mw 151.16), is a non-opiate, non-salicylate analgesic and antipyretic. The structural formula of acetaminophen is:

Active Ingredients: Codeine Phosphate, USP, Butalbital, USP, Caffeine, USP, and Acetaminophen, USP. Inactive Ingredients: FD&C Blue No. 1, FD&C Red No. 3, FD&C Red No. 40, *FD&C Yellow No.5 (see PRECAUTIONS), Gelatin, Microcrystalline Cellulose, Sodium Lauryl Sulfate, Stearic Acid, Talc, Titanium Dioxide.

CLINICAL PHARMACOLOGY

Butalbital, Acetaminophen, Caffeine, and Codeine Phosphate Capsules is a combination drug product intended as a treatment for tension headache. Butalbital, Acetaminophen, Caffeine and Codeine Phosphate Capsules consists of a fixed combination of butalbital 50 mg, acetaminophen 325 mg and caffeine 40 mg. The role each component plays in the relief of the complex of symptoms known as tension headache is incompletely understood.

Pharmacokinetics

The behavior of the individual components is described below.

Codeine

Codeine is readily absorbed from the gastrointestinal tract. It is rapidly distributed from the intravascular spaces to the various body tissues, with preferential uptake by parenchymatous organs such as the liver, spleen and kidney. Codeine crosses the blood-brain barrier, and is found in fetal tissue and breast milk. The plasma concentration does not correlate with brain concentration or relief of pain; however, codeine is not bound to plasma proteins and does not accumulate in body tissues. The plasma half-life is about 2.9 hours. The elimination of codeine is primarily via the kidneys, and about 90% of an oral dose is excreted by the kidneys within 24 hours of dosing. The urinary secretion products consist of free and glucuronide conjugated codeine (about 70%), free and conjugated norcodeine (about 10%), free and conjugated morphine (about 10%), normorphine (about 4%), and hydrocodone (1%). The remainder of the dose is excreted in the feces.

At therapeutic doses, the analgesic effect reaches a peak within 2 hours and persists between 4 and 6 hours. See OVERDOSAGE for toxicity information.

Butalbital

Butalbital is well absorbed from the gastrointestinal tract and is expected to distribute to most tissues in the body. Barbiturates in general may appear in breast milk and readily cross the placental barrier. They are bound to plasma and tissue proteins to a varying degree and binding increases directly as a function of lipid solubility.

Elimination of butalbital is primarily via the kidney (59% to 88% of the dose) as unchanged drug or metabolites. The plasma half-life is about 35 hours. Urinary excretion products include parent drug (about 3.6% of the dose), 5-isobutyl-5-(2,3-dihydroxypropyl) barbituric acid (about 24% of the dose), 5-allyl-5(3-hydroxy-2-methyl-1-propyl) barbituric acid (about 4.8% of the dose), products with the barbituric acid ring hydrolyzed with excretion of urea (about 14% of the dose), as well as unidentified materials. Of the material excreted in the urine, 32% is conjugated.

The in vitro plasma protein binding of butalbital is 45% over the concentration range of 0.5 to 20 mcg/mL. This falls within the range of plasma protein binding (20% to 45%) reported with other barbiturates such as phenobarbital, pentobarbital, and secobarbital sodium. The plasma-to-blood concentration ratio was almost unity indicating that there is no preferential distribution of butalbital into either plasma or blood cells. See OVERDOSAGE for toxicity information.

Caffeine

Like most xanthines, caffeine is rapidly absorbed and distributed in all body tissues and fluids, including the CNS, fetal tissues, and breast milk. Caffeine is cleared through metabolism and excretion in the urine. The plasma half-life is about 3 hours. Hepatic biotransformation prior to excretion results in about equal amounts of 1-methylxanthine and 1-methyluric acid. Of the 70% of the dose that is recovered in the urine, only 3% is unchanged drug. See OVERDOSAGE for toxicity information.

Acetaminophen

Acetaminophen is rapidly absorbed from the gastrointestinal tract and is distributed throughout most body tissues. The plasma half-life is 1.25 to 3 hours, but may be increased by liver damage and following overdosage. Elimination of acetaminophen is principally by liver metabolism (conjugation) and subsequent renal excretion of metabolites. Approximately 85% of an oral dose appears in the urine within 24 hours of administration, most as the glucuronide conjugate, with small amounts of other conjugates and unchanged drug. See OVERDOSAGE for toxicity information.

INDICATIONS

Butalbital, Acetaminophen, Caffeine, and Codeine Phosphate Capsules are indicated for the relief of the symptom complex of tension (or muscle contraction) headache. Evidence supporting the efficacy and safety of Butalbital, Acetaminophen, Caffeine, and Codeine Phosphate Capsules in the treatment of multiple recurrent headaches is unavailable. Caution in this regard is required because codeine and butalbital are habit-forming and potentially abusable.

CONTRAINDICATIONS

This combination product is contraindicated under the following conditions:

- Hypersensitivity or intolerance to acetaminophen, caffeine, butalbital, or codeine.

- Patients with porphyria.

WARNINGS

In the presence of head injury or other intracranial lesions, the respiratory depressant effects of codeine and other narcotics may be markedly enhanced, as well as their capacity for elevating cerebrospinal fluid pressure. Narcotics also produce other CNS depressant effects, such as drowsiness, that may further obscure the clinical course of the patients with head injuries.

Codeine or other narcotics may obscure signs on which to judge the diagnosis or clinical course of patients with acute abdominal conditions. Butalbital and codeine are both habit-forming and potentially abusable.

Consequently, the extended use of this combination product is not recommended.

PRECAUTIONS

General

Butalbital, Acetaminophen, Caffeine, and Codeine Phosphate Capsules should be prescribed with caution in certain special-risk patients such as the elderly or debilitated, and those with severe impairment of renal or hepatic function, head injuries, elevated intracranial pressure, acute abdominal conditions, hypothyroidism, urethral stricture, Addison's disease, or prostatic hypertrophy.

Ultra-rapid Metabolizers of Codeine

Some individuals may be ultra-rapid metabolizers due to a specific CYP2D6*2x2 genotype. These individuals convert codeine into its active metabolite, morphine, more rapidly and completely than other people. This rapid conversion results in higher than expected serum morphine levels. Even at labeled dosage regimens, individuals who are ultra-rapid metabolizers may experience overdose symptoms such as extreme sleepiness, confusion or shallow breathing.

The prevalence of this CYP2D6 phenotype varies widely and has been estimated at 0.5 to 1% in Chinese and Japanese, 0.5 to 1% in Hispanics, 1-10% in Caucasians, 3% in African Americans, and 16-28% in North Africans, Ethiopians and Arabs. Data is not available for other ethnic groups.

When physicians prescribe codeine-containing drugs, they should choose the lowest effective dose for the shortest period of time and should inform their patients about these risks and the signs of morphine overdose. (See PRECAUTIONS, Nursing Mothers)

FD&C Yellow No. 5 (Tartrazine)

This product contains FD&C Yellow No. 5 (tartrazine) which may cause allergic type reactions (including bronchial asthma) in certain susceptible persons. Although the overall incidence of FD&C Yellow No. 5 (tartrazine) sensitivity in the general population is low, it is frequently seen in patients who also have aspirin hypersensitivity.

Information for Patients

Butalbital, Acetaminophen, Caffeine, and Codeine Phosphate Capsules may impair mental and/or physical abilities required for the performance of potentially hazardous tasks such as driving a car or operating machinery. Such tasks should be avoided while taking this combination product. Alcohol and other CNS depressants may produce an additive CNS depression when taken with this combination product and should be avoided. Codeine and butalbital may be habit-forming. Patients should take the drug only for as long as it is prescribed, in the amounts prescribed, and no more frequently than prescribed. For information on use in geriatric patients, see PRECAUTIONS/Geriatric Use.

Caution patients that some people have a variation in a liver enzyme and change codeine into morphine more rapidly and completely than other people. These people are ultra-rapid metabolizers and are more likely to have higher-than-normal levels of morphine in their blood after taking codeine which can result in overdose symptoms such as extreme sleepiness, confusion, or shallow breathing. In most cases, it is unknown if someone is an ultra-rapid codeine metabolizer.

Nursing mothers taking codeine can also have higher morphine levels in their breast milk if they are ultra-rapid metabolizers. These higher levels of morphine in breast milk may lead to life-threatening or fatal side effects in nursing babies. Instruct nursing mothers to watch for signs of morphine toxicity in their infants including increased sleepiness (more than usual), difficulty breastfeeding, breathing difficulties, or limpness. Instruct nursing mothers to talk to the baby's doctor immediately if they notice these signs and, if they cannot reach the doctor right away, to take the baby to an emergency room or call 911 (or local emergency services).

Laboratory Tests

In patients with severe hepatic or renal disease, effects of therapy should be monitored with serial liver and/or renal function tests.

Drug Interactions

The CNS effects of butalbital may be enhanced by monoamine oxidase (MAO) inhibitors. Butalbital, Acetaminophen, Caffeine, and Codeine Phosphate Capsules may enhance the effects of:

- Other narcotic analgesics, alcohol, general anesthetics, tranquilizers such as chlordiazepoxide, sedative-hypnotics, or other CNS depressants, causing increased CNS depression.

Drug/Laboratory Test Interactions

Codeine

Codeine may increase serum amylase levels.

Acetaminophen

Acetaminophen may produce false-positive test results for urinary 5-hydroxyindoleacetic acid.

Carcinogenesis, Mutagenesis, Impairment of Fertility

No adequate studies have been conducted in animals to determine whether acetaminophen, codeine and butalbital have a potential for carcinogenesis or mutagenesis. No adequate studies have been conducted in animals to determine whether acetaminophen and butalbital have a potential for impairment of fertility.

Pregnancy

Teratogenic Effects

Pregnancy Category C

Animal reproduction studies have not been conducted with Butalbital, Acetaminophen, Caffeine, and Codeine Phosphate Capsules. It is also not known whether Butalbital, Acetaminophen, Caffeine, and Codeine Phosphate Capsules can cause fetal harm when administered to a pregnant woman or can affect reproduction capacity. This combination product should be given to a pregnant woman only when clearly needed.

Nonteratogenic Effects

Withdrawal seizures were reported in a two-day-old male infant whose mother had taken a butalbital-containing drug during the last 2 months of pregnancy. Butalbital was found in the infant's serum. The infant was given phenobarbital 5 mg/kg, which was tapered without further seizure or other withdrawal symptoms.

Labor and Delivery

Use of codeine during labor may lead to respiratory depression in the neonate.

Nursing Mothers

Caffeine, barbiturates, acetaminophen and codeine are excreted in breast milk in small amounts, but the significance of their effects on nursing infants is not known. Because of potential for serious adverse reactions in nursing infants from Butalbital, Acetaminophen, Caffeine and Codeine Phosphate Capsules, a decision should be made whether to discontinue nursing or to discontinue the drug, taking into account the importance of the drug to the mother.

Codeine is secreted into human milk. In women with normal codeine metabolism (normal CYP2D6 activity), the amount of codeine secreted into human milk is low and dose-dependent. Despite the common use of codeine products to manage postpartum pain, reports of adverse events in infants are rare. However, some women are ultra-rapid metabolizers of codeine. These women achieve higher-than-expected serum levels of codeine's active metabolite, morphine, leading to higher-than-expected levels of morphine in breast milk and potentially dangerously high serum morphine levels in their breastfed infants. Therefore, maternal use of codeine can potentially lead to serious adverse reactions, including death, in nursing infants.

The prevalence of this CYP2D6 phenotype varies widely and has been estimated at 0.5 to 1% in Chinese and Japanese, 0.5 to 1% in Hispanics, 1-10% in Caucasians, 3% in African Americans, and 16-28% in North Africans, Ethiopians and Arabs. Data is not available for other ethnic groups.

The risk of infant exposure to codeine and morphine through breast milk should be weighed against the benefits of breastfeeding for both the mother and baby. Caution should be exercised when codeine is administered to a nursing woman. If a codeine containing product is selected, the lowest dose should be prescribed for the shortest period of time to achieve the desired clinical effect. Mothers using codeine should be informed about when to seek immediate medical care and how to identify the signs and symptoms of neonatal toxicity, such as drowsiness or sedation, difficulty breastfeeding, breathing difficulties, and decreased tone, in their baby. Nursing mothers who are ultra-rapid metabolizers may also experience overdose symptoms such as extreme sleepiness, confusion or shallow breathing. Prescribers should closely monitor mother-infant pairs and notify treating pediatricians about the use of codeine during breastfeeding. (See PRECAUTIONS, General, Ultra-rapid Metabolizers of Codeine)

Pediatric Use

Safety and effectiveness in pediatric patients have not been established.

Geriatric Use

Clinical studies of Butalbital, Acetaminophen, Caffeine, and Codeine Phosphate Capsules did not include sufficient numbers of subjects aged 65 and over to determine whether they respond differently from younger subjects. Other reported clinical experience has not identified differences in responses between the elderly and younger patients. In general, dose selection for an elderly patient should be cautious, usually starting at the low end of the dosing range, reflecting the greater frequency of decreased hepatic, renal, or cardiac function, and of concomitant disease or other drug therapy. Butalbital is known to be substantially excreted by the kidney, and the risk of toxic reactions to this drug may be greater in patients with impaired renal function. Because elderly patients are more likely to have decreased renal function, care should be taken in dose selection, and it may be useful to monitor renal function.

ADVERSE REACTIONS

Frequently Observed: The most frequently reported adverse reactions are drowsiness, lightheadedness, dizziness, sedation, shortness of breath, nausea, vomiting, abdominal pain, and intoxicated feeling.

Infrequently Observed: All adverse events tabulated below are classified as infrequent.

Central Nervous: headache, shaky feeling, tingling, agitation, fainting, fatigue, heavy eyelids, high energy, hot spells, numbness, sluggishness, seizure. Mental confusion, excitement or depression can also occur due to intolerance, particularly in elderly or debilitated patients, or due to overdosage of butalbital.

Autonomic Nervous: dry mouth, hyperhidrosis.

Gastrointestinal: difficulty swallowing, heartburn, flatulence, constipation.

Cardiovascular: tachycardia.

Musculoskeletal: leg pain, muscle fatigue.

Genitourinary: diuresis.

Miscellaneous: pruritus, fever, earache, nasal congestion, tinnitus, euphoria, allergic reactions.

The following adverse reactions have been voluntarily reported as temporally associated with Fiorinal® [Fiorinal® is a registered trademark of Watson Pharmaceuticals, Inc.] with Codeine, a related product containing aspirin, butalbital, caffeine, and codeine phosphate.

Central Nervous: abuse, addiction, anxiety, disorientation, hallucination, hyperactivity, insomnia, libido decrease, nervousness, neuropathy, psychosis, sexual activity increase, slurred speech, twitching, unconsciousness, vertigo.

Autonomic Nervous: epistaxis, flushing, miosis, salivation.

Gastrointestinal: anorexia, appetite increased, diarrhea, esophagitis, gastroenteritis, gastrointestinal spasms, hiccup, mouth burning, pyloric ulcer.

Cardiovascular: chest pain, hypotensive reaction, palpitations, syncope.

Skin: erythema, erythema multiforme, exfoliative dermatitis, hives, rash, toxic epidermal necrolysis.

Urinary: kidney impairment, urinary difficulty.

Miscellaneous: allergic reaction, anaphylactic shock, cholangiocarcinoma, drug interaction with erythromycin (stomach upset), edema.

The following adverse drug events may be borne in mind as potential effects of the components of Butalbital, Acetaminophen, Caffeine, and Codeine Phosphate Capsules. Potential effects of high dosage are listed in the OVERDOSAGE section.

Acetaminophen: allergic reactions, rash, thrombocytopenia, agranulocytosis.

Caffeine: cardiac stimulation, irritability, tremor, dependence, nephrotoxicity, hyperglycemia.

Codeine: nausea, vomiting, drowsiness, lightheadedness, constipation, pruritus. Several cases of dermatological reactions, including toxic epidermal necrolysis and erythema multiforme, have been reported for Butalbital, Acetaminophen, Caffeine and Codeine Phosphate Capsules, USP.

DRUG ABUSE AND DEPENDENCE

Controlled Substance

Butalbital, Acetaminophen, Caffeine, and Codeine Phosphate Capsules is controlled by the Drug Enforcement Administration and is classified under Schedule III.

Abuse and Dependence

Codeine

Codeine can produce drug dependence of the morphine type and, therefore, has the potential for being abused. Psychological dependence, physical dependence, and tolerance may develop upon repeated administration and it should be prescribed and administered with the same degree of caution appropriate to the use of other oral narcotic medications.

Butalbital

Barbiturates may be habit-forming

Tolerance, psychological dependence, and physical dependence may occur especially following prolonged use of high doses of barbiturates. The average daily dose for the barbiturate addict is usually about 1,500 mg. As tolerance to barbiturates develops, the amount needed to maintain the same level of intoxication increases; tolerance to a fatal dosage, however, does not increase more than two-fold. As this occurs, the margin between an intoxication dosage and fatal dosage becomes smaller. The lethal dose of a barbiturate is far less if alcohol is also ingested. Major withdrawal symptoms (convulsions and delirium) may occur within 16 hours and last up to 5 days after abrupt cessation of these drugs. Intensity of withdrawal symptoms gradually declines over a period of approximately 15 days. Treatment of barbiturate dependence consists of cautious and gradual withdrawal of the drug.

Barbiturate-dependent patients can be withdrawn by using a number of different withdrawal regimens. One method involves initiating treatment at the patient's regular dosage level and gradually decreasing the daily dosage as tolerated by the patient.

OVERDOSAGE

Following an acute overdosage of Butalbital, Acetaminophen, Caffeine, and Codeine Phosphate Capsules, toxicity may result from the barbiturate, the codeine, or the acetaminophen. Toxicity due to the caffeine is less likely, due to the relatively small amounts in this formulation.

Signs and Symptoms

Toxicity from barbiturate poisoning includes drowsiness, confusion, and coma; respiratory depression; hypotension; and hypovolemic shock. Toxicity from codeine poisoning includes the opioid triad of: pinpoint pupils, depression of respiration, and loss of consciousness. Convulsions may occur. In acetaminophen overdosage : dose-dependent, potentially fatal hepatic necrosis is the most serious adverse effect. Renal tubular necroses, hypoglycemic coma, and thrombocytopenia may also occur. Early symptoms following a potentially hepatotoxic overdose may include: nausea, vomiting, diaphoresis, and general malaise. Clinical and laboratory evidence of hepatic toxicity may not be apparent until 48 to 72 hours post-ingestion. In adults hepatic toxicity has rarely been reported with acute overdoses of less than 10 grams, or fatalities with less than 15 grams. Acute caffeine poisoning may cause insomnia, restlessness, tremor, and delirium, tachycardia, and extrasystoles.

Treatment

A single or multiple overdose with Butalbital, Acetaminophen, Caffeine, and Codeine Phosphate Capsules is a potentially lethal polydrug overdose, and consultation with a regional poison control center is recommended. Immediate treatment includes support of cardiorespiratory function and measures to reduce drug absorption. Vomiting should be induced mechanically, or with syrup of ipecac, if the patient is alert (adequate pharyngeal and laryngeal reflexes). Oral activated charcoal (1 g/kg) should follow gastric emptying. The first dose should be accompanied by an appropriate cathartic. If repeated doses are used, the cathartic might be included with alternate doses as required. Hypotension is usually hypovolemic and should respond to fluids. The value of vasopressor agents such as norepinephrine or phenylephrine hydrochloride in treating hypotension is questionable since they increase vasoconstriction and decrease blood flow. However, if prolonged support of blood pressure is required, norepinephrine bitartrate (Levophed®) [Levophed® is a registered Trademark of Hospira, Inc.] may be given I.V. with the usual precautions and serial blood pressure monitoring. A cuffed endotracheal tube should be inserted before gastric lavage of the unconscious patient and, when necessary, to provide assisted respiration. If renal function is normal, forced diuresis may aid in the elimination of the barbiturate. Alkalinization of the urine increases renal excretion of some barbiturates, especially phenobarbital.

Meticulous attention should be given to maintaining adequate pulmonary ventilation. In severe cases of intoxication, peritoneal dialysis, or preferably hemodialysis may be considered. If hypoprothrombinemia occurs due to acetaminophen overdose, vitamin K should be administered intravenously.

Naloxone, a narcotic antagonist, can reverse respiratory depression and coma associated with opioid overdose. Naloxone 0.4 to 2 mg is given parenterally. Since the duration of action of codeine may exceed that of the naloxone, the patient should be kept under continuous surveillance and repeated doses of the antagonist should be administered as needed to maintain adequate respiration. A narcotic antagonist should not be administered in the absence of clinically significant respiratory or cardiovascular depression.

If the dose of acetaminophen may have exceeded 140 mg/kg, N-acetyl-cysteine should be administered as early as possible. Serum acetaminophen levels should be obtained, since levels 4 or more hours following ingestion help predict acetaminophen toxicity. Do not await acetaminophen assay results before initiating treatment. Hepatic enzymes should be obtained initially, and repeated at 24-hour intervals. Methemoglobinemia over 30% should be treated with methylene blue by slow intravenous administration.

Toxic doses (for adults)

Butalbital: toxic dose 1 g (20 capsules)

Acetaminophen: toxic dose 10 g (30 capsules)

Caffeine: toxic dose 1 g (25 capsules)

Codeine: toxic dose 240 mg (8 capsules).

DOSAGE AND ADMINISTRATION

One or two capsules every four hours. Total daily dosage should not exceed six capsules.

Extended and repeated use of this combination product is not recommended because of the potential for physical dependence.

HOW SUPPLIED

Butalbital, Acetaminophen, Caffeine, and Codeine Phosphate Capsules: Dark blue, opaque cap with a gray, opaque body, and body is imprinted with "B 073" in black ink.

Bottles of 100's (NDC 51991-073-01)

Store and Dispense

Store at 20° to 25°C (68° to 77°F) in a tight, light-resistant container. [see USP Controlled Room Temperature].

Manufactured by:
Nexgen Pharma, Inc.
Irvine, CA 92614

Distributed by:
Breckenridge Pharmaceutical, Inc.
Boca Raton, FL 33847

6670(Rev. 10/08)

PRINCIPAL DISPLAY PANEL - 100 Capsule Bottle

NDC 68258-2012-XX
NDC 68258-2012-09

Butalbital, Acetaminophen, Caffeine, and Codeine Phosphate Capsules
CIII

Codeine Phosphate, USP ........................................ | 30 mg
Butalbital, USP ........................................................ | 50 mg
Caffeine, USP ......................................................... | 40 mg
Acetaminophen, USP .............................................. | 325 mg

Rx Only
90 Capsules